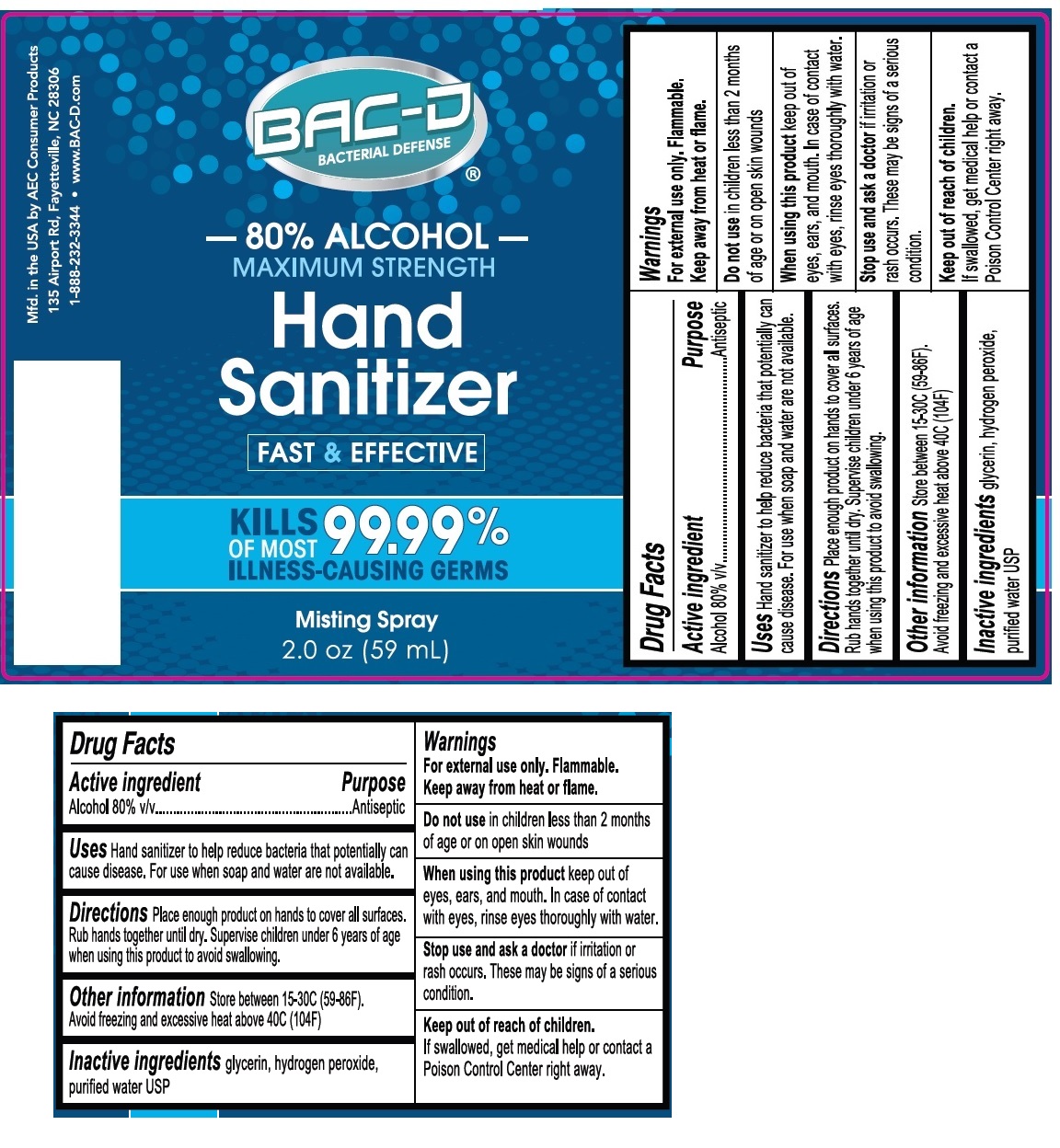 DRUG LABEL: BAC-D Hand Sanitizer
NDC: 86089-900 | Form: SPRAY
Manufacturer: AEC CONSUMER PRODUCTS
Category: otc | Type: HUMAN OTC DRUG LABEL
Date: 20220103

ACTIVE INGREDIENTS: ALCOHOL 80 mL/100 mL
INACTIVE INGREDIENTS: GLYCERIN; HYDROGEN PEROXIDE; WATER

BAC-D® Hand Sanitizer

Active ingredient

Alcohol 80% v/v

Purpose

Antiseptic

INDICATIONS AND USAGE

Uses Hand sanitizer to help reduce bacteria that potentially can cause disease. For use when soap and water are not available.

DOSAGE AND ADMINISTRATION

Directions Place enough product on hands to cover all surfaces. Rub hands together until dry. Supervise children under 6 years of age when using this product to avoid swallowing

Other information Store between 15-30C (59-86F). Avoid freezing and excessive heat above 40C (104F)

Inactive ingredients glycerin, hydrogen peroxide, purified water USP

Warnings

For external use only. Flammable. Keep away from heat or flame.

Do not use in children less than 2 months of age or on open skin wounds

When using this product keep out of eyes, ears, and mouth. In case of contact with eyes, rinse thoroughly with water.

Stop use and ask a doctor if irritation or rash occurs. These may be signs of a serious condition.

Keep out of reach of children. If swallowed, get medical help or contact a Poison Control Center right away.

Mfd. in the USA by AEC Consumer Products

135 Airport Rd, Fayetteville, NC 28306

1-888-232-3344 • www.BAC-D.com

80% ALCOHOL

MAXIMUM STRENGTH

FAST & EFFECTIVE

KILLS 99.99% OF MOST ILLNESS-CAUSING GERMS

Misting Spray